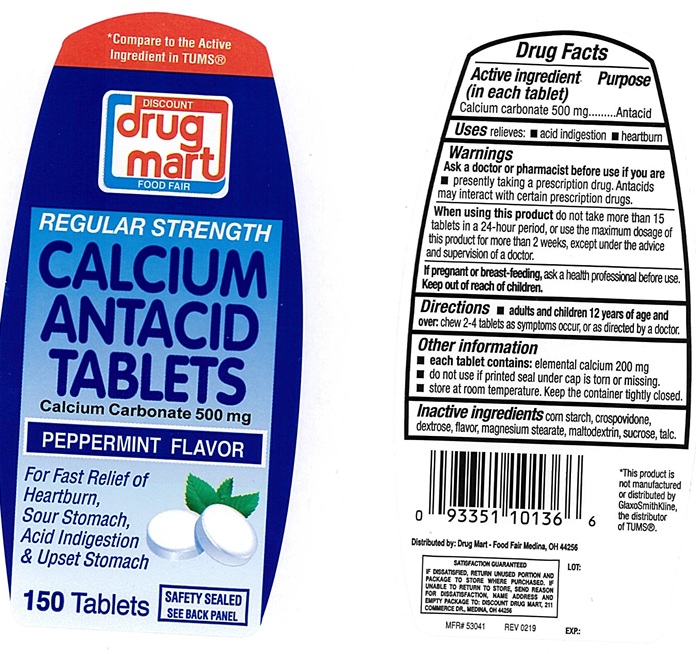 DRUG LABEL: Regular Strength Antacid Peppermint
NDC: 53943-117 | Form: TABLET, CHEWABLE
Manufacturer: Discount Drug Mart, Inc
Category: otc | Type: Human OTC Drug Label
Date: 20250220

ACTIVE INGREDIENTS: CALCIUM CARBONATE 500 mg/1 1
INACTIVE INGREDIENTS: STARCH, CORN; DEXTROSE, UNSPECIFIED FORM; MAGNESIUM STEARATE; MALTODEXTRIN; SUCROSE; TALC; CROSPOVIDONE, UNSPECIFIED

Regular Strength Antacid peppermint Chewable Tablets

ACTIVE INGREDIENT (in each tablet)

Calcium carbonate 500 mg

PURPOSE

Antacid

USES

relieves:

- acid indigestion
- heartburn

WARNINGS

.

ASK A DOCTOR OR PHARMACIST BEFORE USE IF YOU ARE

- presently taking a prescription drug. Antacids may interact with certain prescription drugs.

WHEN USING THIS PRODUCT

do not take more than 15 tablets in a 24-hour period, or use the maximum dosage of this product for more than 2 weeks, except under the advice and supervision of a doctor.

IF PREGNANT OR BREAST FEEDING,

ask a health professional before use.

KEEP OUT OF REACH OF CHILDREN

.

DIRECTIONS

- adults and children 12 years of age and over:
- chew 2-4 tablets as symptoms occur, or as directed by a doctor.

OTHER INFORMATION

- each tablet contains: elemental calcium 200 mg
- do not use if printed seal under the cap is torn or missing.
- store at room temperature. keep the container tightly closed.

INACTIVE INGREDIENTS

corn starch, crospovidone, dextrose, flavor, magnesium stearate, maltodextrin, sucrose, talc.

PRINCIPAL DISPLAY PANEL

*compare to the Active Ingredient in TUMS®

DISCOUNT drug mart

FOOD FAIR

NDC 53943-117-17

REGULAR STRENGTH

CALCIUM ANTACID TABLETS

Calcium Carbonate 500 mg

PEPPERMINT FLAVOR

For Fast Relief of Heartburn,

Sour Stomach,

Acid Indigestion

& Upset Stomach

150 Tablets